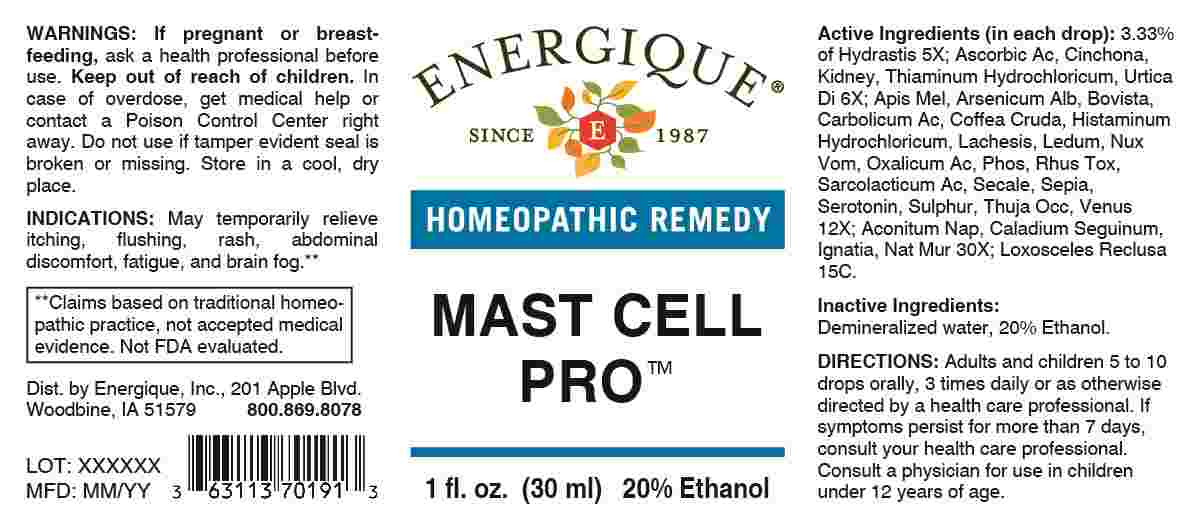 DRUG LABEL: Mast Cell Pro
NDC: 44911-0723 | Form: LIQUID
Manufacturer: Energique, Inc.
Category: homeopathic | Type: HUMAN OTC DRUG LABEL
Date: 20241211

ACTIVE INGREDIENTS: GOLDENSEAL 5 [hp_X]/1 mL; ASCORBIC ACID 6 [hp_X]/1 mL; CINCHONA OFFICINALIS BARK 6 [hp_X]/1 mL; PORK KIDNEY 6 [hp_X]/1 mL; THIAMINE HYDROCHLORIDE 6 [hp_X]/1 mL; URTICA DIOICA WHOLE 6 [hp_X]/1 mL; APIS MELLIFERA 12 [hp_X]/1 mL; ARSENIC TRIOXIDE 12 [hp_X]/1 mL; LYCOPERDON UTRIFORME FRUITING BODY 12 [hp_X]/1 mL; PHENOL 12 [hp_X]/1 mL; ARABICA COFFEE BEAN 12 [hp_X]/1 mL; HISTAMINE DIHYDROCHLORIDE 12 [hp_X]/1 mL; LACHESIS MUTA VENOM 12 [hp_X]/1 mL; RHODODENDRON TOMENTOSUM LEAFY TWIG 12 [hp_X]/1 mL; STRYCHNOS NUX-VOMICA SEED 12 [hp_X]/1 mL; OXALIC ACID DIHYDRATE 12 [hp_X]/1 mL; PHOSPHORUS 12 [hp_X]/1 mL; TOXICODENDRON PUBESCENS LEAF 12 [hp_X]/1 mL; LACTIC ACID, L- 12 [hp_X]/1 mL; CLAVICEPS PURPUREA SCLEROTIUM 12 [hp_X]/1 mL; SEPIA OFFICINALIS JUICE 12 [hp_X]/1 mL; SEROTONIN HYDROCHLORIDE 12 [hp_X]/1 mL; SULFUR 12 [hp_X]/1 mL; THUJA OCCIDENTALIS LEAFY TWIG 12 [hp_X]/1 mL; NORTHERN QUAHOG 12 [hp_X]/1 mL; ACONITUM NAPELLUS WHOLE 30 [hp_X]/1 mL; DIEFFENBACHIA SEGUINE WHOLE 30 [hp_X]/1 mL; STRYCHNOS IGNATII SEED 30 [hp_X]/1 mL; SODIUM CHLORIDE 30 [hp_X]/1 mL; LOXOSCELES RECLUSA 15 [hp_C]/1 mL
INACTIVE INGREDIENTS: WATER; ALCOHOL

DRUG FACTS:

ACTIVE INGREDIENT:

(in each drop): 3.33% of Hydrastis Canadensis 5X; Ascorbicum Acidum 6X, Cinchona Officinalis 6X, Kidney 6X, Thiaminum Hydrochloricum 6X, Urtica Dioica 6X; Apis Mellifica 12X, Arsenicum Album 12X, Bovista 12X, Carbolicum Acidum 12X, Coffea Cruda 12X, Histaminum Hydrochloricum 12X, Lachesis Mutus 12X, Ledum Palustre 12X, Nux Vomica 12X, Oxalicum Acidum 12X, Phosphorus 12X, Rhus Tox 12X, Sarcolacticum Acidum 12X, Secale Cornutum 12X, Sepia 12X, Serotonin 12X, Sulphur 12X, Thuja Occidentalis 12X, Venus Mercenaria 12X; Aconitum Napellus 30X, Caladium Seguinum 30X, Ignatia Amara 30X, Natrum Muriaticum 30X; Loxosceles Reclusa 15C.

PURPOSE:

May temporarily relieve itching, flushing, rash, abdominal discomfort, fatigue, and brain fog.**

**Claims based on traditional homeopathic practice, not accepted medical evidence. Not FDA evaluated.

WARNINGS:

If pregnant or breast-feeding, ask a health professional before use.

Keep out of reach of children. In case of overdose, get medical help or contact a Poison Control Center right away.

Do not use if tamper evident seal is broken or missing.

Store in a cool, dry place.

KEEP OUT OF REACH OF CHILDREN:

In case of overdose, get medical help or contact a Poison Control Center right away.

DIRECTIONS:

Adults and children 5 to 10 drops orally, 3 times daily or as otherwise directed by a health care professional. If symptoms persist for more than 7 days, consult your health care professional. Consult a physician for use in children under 12 years of age.

INDICATIONS:

May temporarily relieve itching, flushing, rash, abdominal discomfort, fatigue, and brain fog.**

**Claims based on traditional homeopathic practice, not accepted medical evidence. Not FDA evaluated.

INACTIVE INGREDIENTS:

Demineralized water, 20% Ethanol.

QUESTIONS:

Dist. by Energique, Inc.

201 Apple Blvd

Woodbine, IA 51579

800.869.8078

PACKAGE LABEL DISPLAY:

ENERGIQUE
SINCE 1987
HOMEOPATHIC REMEDY
MAST CELL PRO
1 fl. oz. (30 ml)